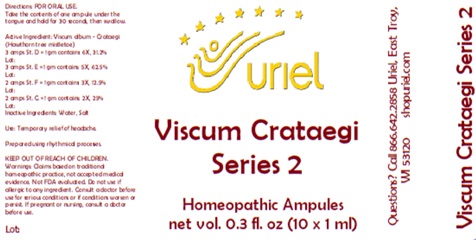 DRUG LABEL: Viscum Crataegi Series 2
NDC: 48951-9208 | Form: LIQUID
Manufacturer: Uriel Pharmacy Inc.
Category: homeopathic | Type: HUMAN OTC DRUG LABEL
Date: 20250107

ACTIVE INGREDIENTS: VISCUM ALBUM FRUITING TOP 2 [hp_X]/1 mL
INACTIVE INGREDIENTS: WATER; SODIUM CHLORIDE

Viscum Crataegi Series 2

INDICATIONS AND USAGE

Directions: FOR ORAL USE.

DOSAGE AND ADMINISTRATION

Take the contents of one ampule under the tongue and hold for 30 seconds, then swallow.

Active Ingredient: Viscum album - Crataegi (Hawthorn tree mistletoe)
3 amps St. D = 1 gm contains: 6X, 31.2%
3 amps St. E = 1 gm contains: 5X, 62.5%
2 amps St. F = 1 gm contains: 3X, 12.5%
2 amps St. G = 1 gm contains: 2X, 25%

Inactive Ingredients: Water, Salt

Prepared using rhythmical processes.

PURPOSE

Use: Temporary relief of headache.

KEEP OUT OF REACH OF CHILDREN.

WARNINGS

Warnings: Claims based on traditional homeopathic practice, not accepted medical evidence. Not FDA evaluated. Do not use if allergic to any ingredient. Consult a doctor before use for serious conditions or if conditions worsen or persist. If pregnant or nursing, consult a doctor before use.

QUESTIONS

Questions? Call 866.642.2858 Uriel, East Troy, WI 53120 shopuriel.com